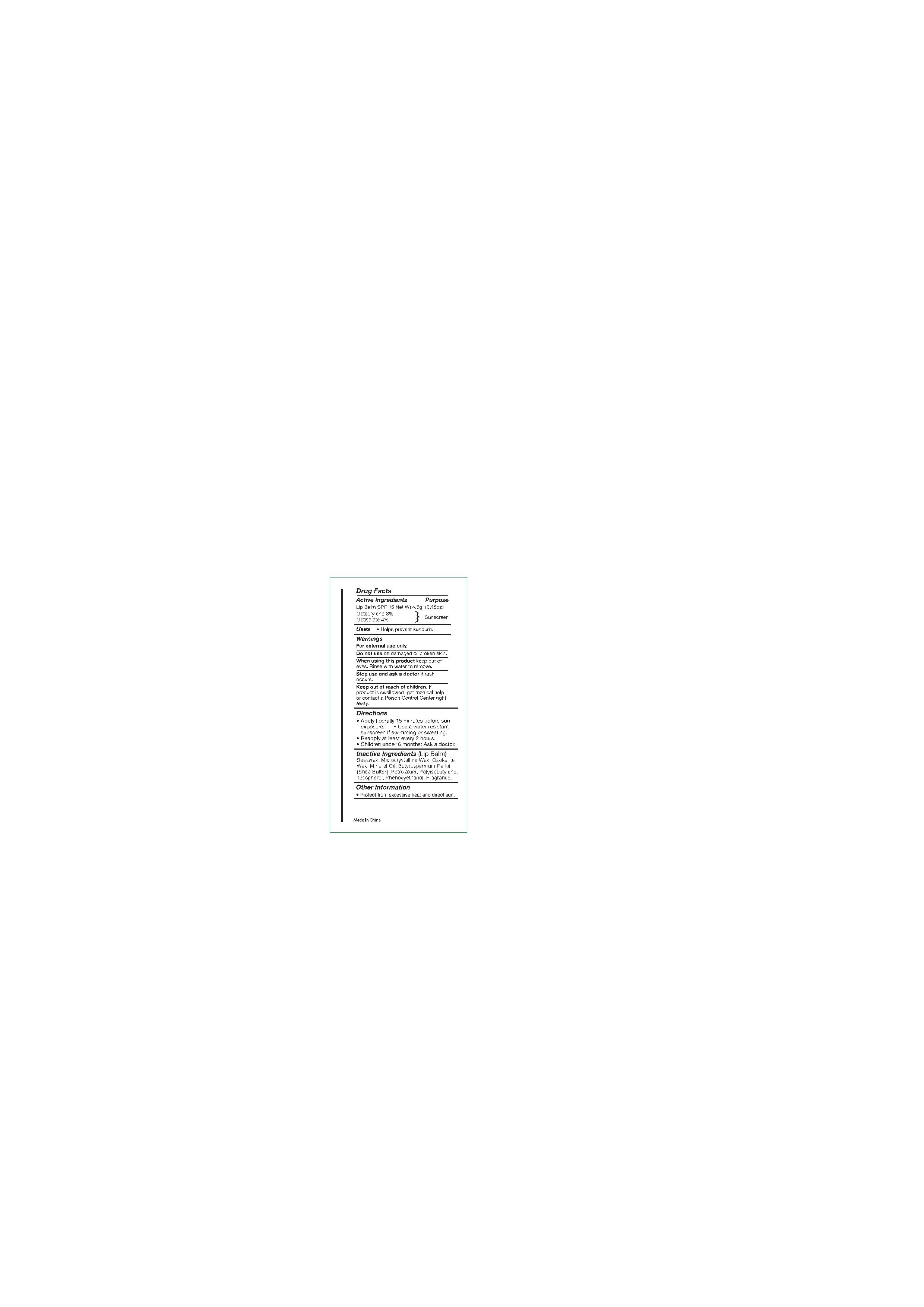 DRUG LABEL: lip balm SPF15( CB400)
NDC: 82953-042 | Form: LIPSTICK
Manufacturer: Cosmuses Cosmetics (Ningbo) Co., Ltd.
Category: otc | Type: HUMAN OTC DRUG LABEL
Date: 20250328

ACTIVE INGREDIENTS: OCTOCRYLENE 8 g/100 g; OCTISALATE 4 g/100 g
INACTIVE INGREDIENTS: PETROLATUM; MINERAL OIL; BEESWAX; CERESIN; PHENOXYETHANOL; FRAGRANCE 13576; MICROCRYSTALLINE WAX; POLYISOBUTYLENE (1000 MW); TOCOPHEROL; BUTYROSPERMUM PARKII (SHEA) BUTTER

lip balm SPF15 (CB400)

Drug Facts

Active ingredients

Octocrylene 8%

Octisalate 4%

Purpose

Sunscreen

Uses

- Helps prevent sunburn

warnings

For external use only.

Do not use on damaged or broken skin.

Stop use and ask a doctor if rash occurs.

When using this product keep out of eyes. Rinse with water to remove.

Keep out of reach of children. If swallowed, get medical help or contact a Poison Control Center right away.

Directions

- Apply liberally 15minutes before sun exposure
- Use a water resistant sunscreen if swimming or sweating.
- Reapply at least every 2 hours.
- Children under 6 months of age: Ask a doctor.

Inactive ingredients

Beeswax, Microcrystalline wax, Ozokerite wax, Mineral Oil, Butyrospermum Parkii (Shea) Butter, Petrolatum, Polyisobutene, Tocopherol, Phenoxyethanol, Fragrance

other information

Protect from excessive heat and direct sun.